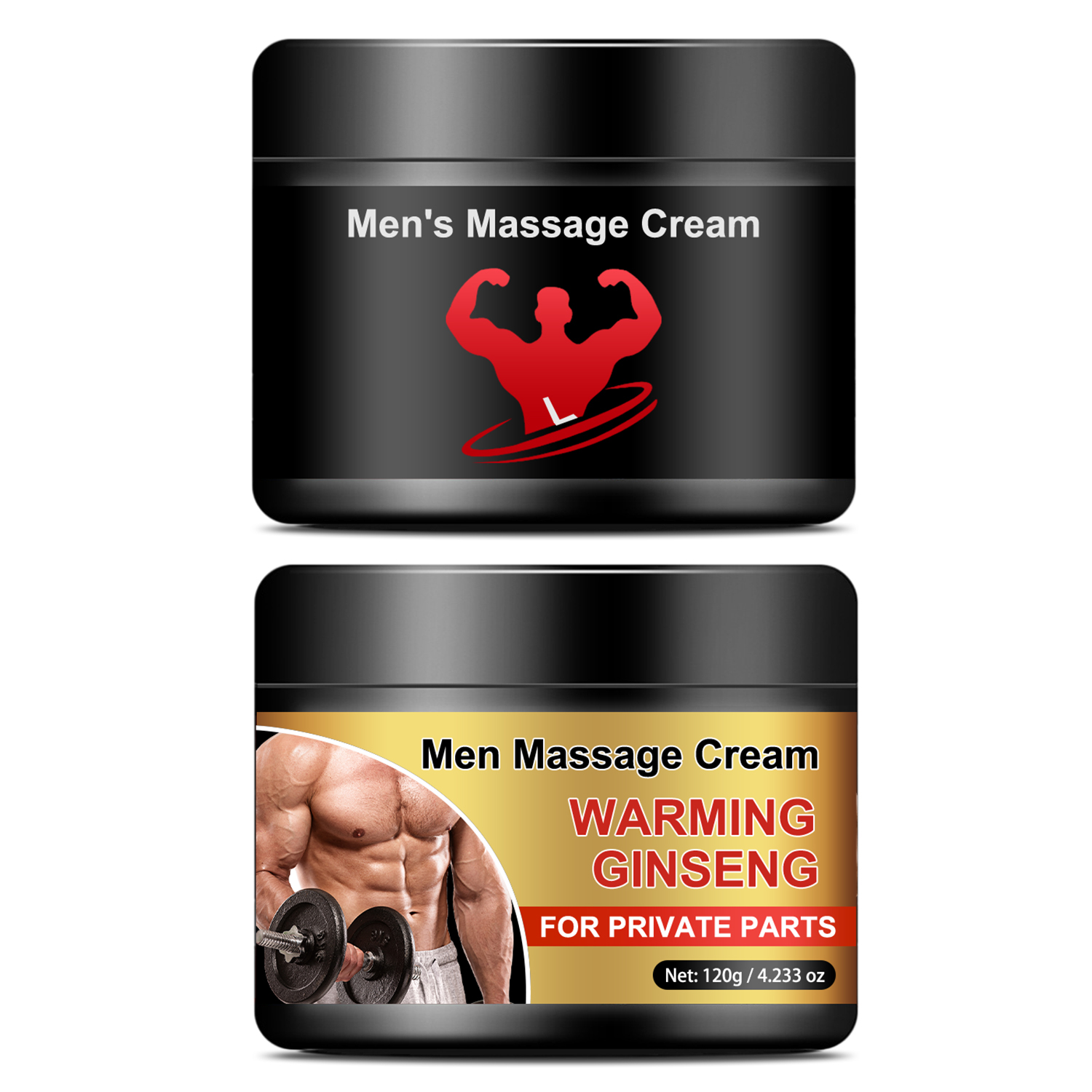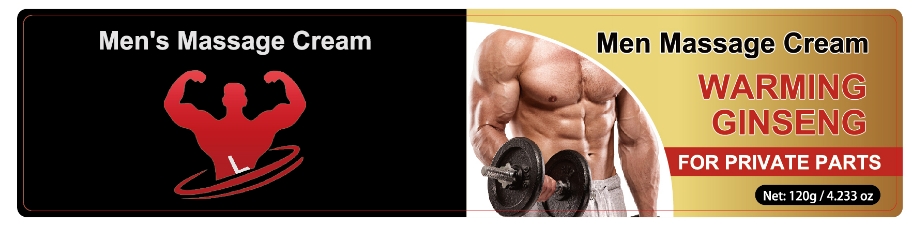 DRUG LABEL: Mens Massage Cream
NDC: 84025-150 | Form: CREAM
Manufacturer: Guangzhou Yanxi Biotechnology Co.. Ltd
Category: otc | Type: HUMAN OTC DRUG LABEL
Date: 20240817

ACTIVE INGREDIENTS: GLYCERIN 5 mg/120 g; PANTHENOL 3 mg/120 g
INACTIVE INGREDIENTS: WATER

DOSAGE AND ADMINISTRATION

Cream for skin massage

WARNINGS

Keep out of children

INACTIVE INGREDIENT

Aqua

INDICATIONS AND USAGE

For daily men's skin care

Keep out of children

PURPOSE

Moisturizing and maintaining skin